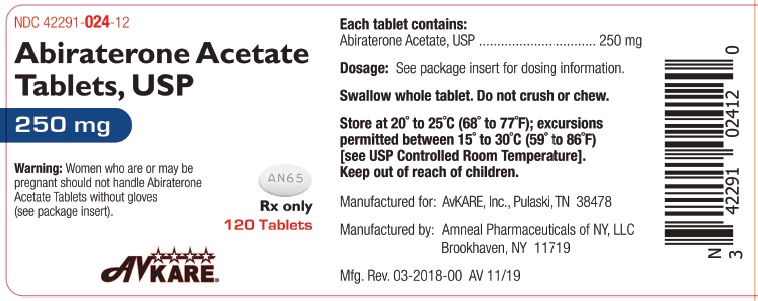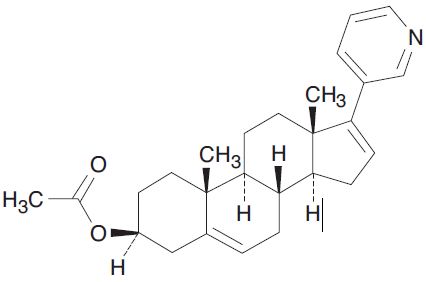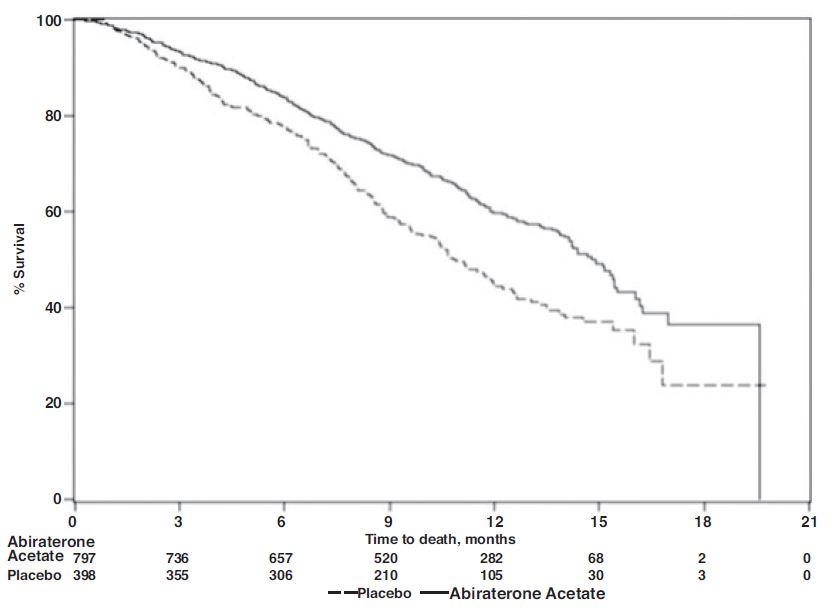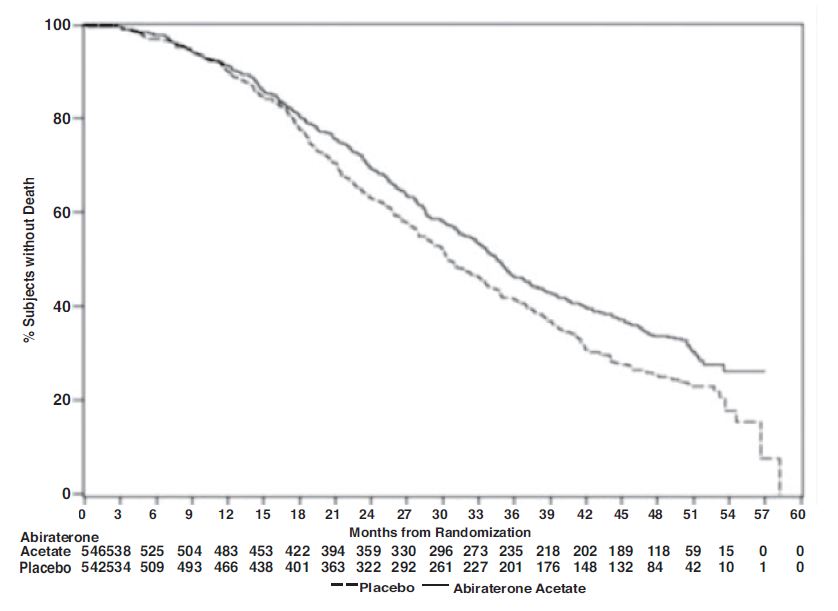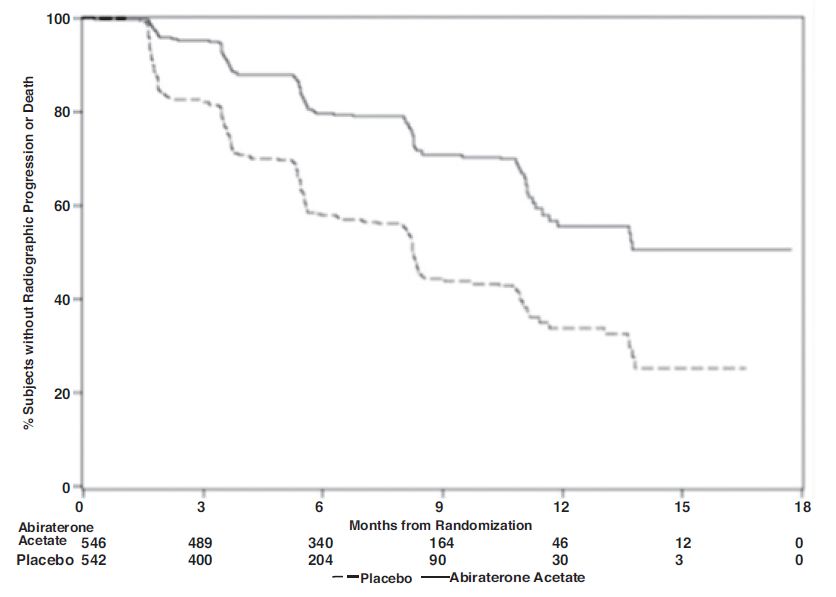 DRUG LABEL: Abiraterone Acetate
NDC: 42291-024 | Form: TABLET
Manufacturer: AvKARE
Category: prescription | Type: HUMAN PRESCRIPTION DRUG LABEL
Date: 20260113

ACTIVE INGREDIENTS: ABIRATERONE ACETATE 250 mg/1 1
INACTIVE INGREDIENTS: SILICON DIOXIDE; CROSCARMELLOSE SODIUM; LACTOSE MONOHYDRATE; MAGNESIUM STEARATE; POVIDONE; SODIUM LAURYL SULFATE; CELLULOSE, MICROCRYSTALLINE

HIGHLIGHTS OF PRESCRIBING INFORMATION

Abiraterone Acetate Tablets, USP
Rx Only
These highlights do not include all the information needed to use ABIRATERONE ACETATE TABLETS safely and effectively. See full prescribing information for ABIRATERONE ACETATE TABLETS.
ABIRATERONE ACETATE tablets, for oral use
Initial U.S. Approval: 2011

RECENT MAJOR CHANGES

Dosage and Administration (2) 02/2018
Warnings and Precautions (5) 02/2018

1 INDICATIONS AND USAGE

Abiraterone acetate tablets are a CYP17 inhibitor indicated in combination with prednisone for the treatment of patients with

- metastatic castration-resistant prostate cancer (CRPC). (1)

2 DOSAGE AND ADMINISTRATION

Metastatic castration-resistant prostate cancer:

- Abiraterone acetate tablets 1,000 mg orally once daily with prednisone 5 mg orally twice daily. (2.1)
  Patients receiving abiraterone acetate tablets should also receive a gonadotropin-releasing hormone (GnRH) analog concurrently or should have had bilateral orchiectomy. Abiraterone acetate tablets must be taken on an empty stomach with water at least 1 hour before or 2 hours after a meal. Do not crush or chew tablets. (2.3)
  Dose Modification:
- For patients with baseline moderate hepatic impairment (Child-Pugh Class B), reduce the abiraterone acetate tablets starting dose to 250 mg once daily. (2.4)
- For patients who develop hepatotoxicity during treatment, hold abiraterone acetate tablets until recovery. Retreatment may be initiated at a reduced dose. Abiraterone acetate tablets should be discontinued if patients develop severe hepatotoxicity. (2.4)

3 DOSAGE FORMS AND STRENGTHS

- Uncoated Tablet 250 mg (3)

4 CONTRAINDICATIONS

- Pregnancy. (4,8.1)

5 WARNINGS AND PRECAUTIONS

- Mineralocorticoid excess: Closely monitor patients with cardiovascular disease. Control hypertension and correct hypokalemia before treatment. Monitor blood pressure, serum potassium and symptoms of fluid retention at least monthly. (5.1)
- Adrenocortical insufficiency: Monitor for symptoms and signs of adrenocortical insufficiency. Increased dosage of corticosteroids may be indicated before, during and after stressful situations. (5.2)
- Hepatotoxicity: Can be severe and fatal. Monitor liver function and modify, interrupt, or discontinue abiraterone acetate dosing as recommended. (5.3)

6 ADVERSE REACTIONS

The most common adverse reactions (≥10%) are fatigue, arthralgia, hypertension, nausea, edema, hypokalemia, hot flush, diarrhea, vomiting, upper respiratory infection, cough, and headache. (6.1)

The most common laboratory abnormalities (>20%) are anemia, elevated alkaline phosphatase, hypertriglyceridemia, lymphopenia, hypercholesterolemia, hyperglycemia, and hypokalemia. (6.1)

To report SUSPECTED ADVERSE REACTIONS, contact AvKARE at 1-855-361-3993 or FDA at
1-800-FDA-1088 or www.fda.gov/medwatch.

7 DRUG INTERACTIONS

- CYP3A4 Inducers: Avoid concomitant strong CYP3A4 inducers during abiraterone acetate tablets treatment. If a strong CYP3A4 inducer must be co-administered, increase the abiraterone acetate tablets dosing frequency. (2.5,7.1)
- CYP2D6 Substrates: Avoid co-administration of abiraterone acetate tablets with CYP2D6 substrates that have a narrow therapeutic index. If an alternative treatment cannot be used, exercise caution and consider a dose reduction of the concomitant CYP2D6 substrate. (7.2)

8 USE IN SPECIFIC POPULATIONS

- Females and Males of Reproductive Potential: Advise males with female partners of reproductive potential to use effective contraception. (8.3)
- Do not use abiraterone acetate tablets in patients with baseline severe hepatic impairment (Child-Pugh Class C). (8.6)

FULL PRESCRIBING INFORMATION

RECENT MAJOR CHANGES

Dosage and Administration. (2.2) 05/2016

Warnings and Precautions. (5.3) 05/2016

1 INDICATIONS AND USAGE

Abiraterone acetate tablets are indicated in combination with prednisone for the treatment of patients with

- Metastatic castration-resistant prostate cancer (CRPC)

2 DOSAGE AND ADMINISTRATION

2.1 Recommended Dose for metastatic CRPC

The recommended dose of abiraterone acetate tablets are 1,000 mg (four 250 mg tablets) orally once daily with prednisone 5 mg orally twice daily.

2.3 Important Administration Instructions

Patients receiving abiraterone acetate tablets should also receive a gonadotropin-releasing hormone (GnRH) analog concurrently or should have had bilateral orchiectomy. Abiraterone acetate tablets must be taken on an empty stomach, either one hour before or two hours after a meal [see Clinical Pharmacology (12.3)]. The tablets should be swallowed whole with water. Do not crush or chew tablets.

2.4 Dose Modification Guidelines in Hepatic Impairment and Hepatotoxicity

Hepatic Impairment

In patients with baseline moderate hepatic impairment (Child-Pugh Class B), reduce the recommended dose of abiraterone acetate tablets to 250 mg once daily. In patients with moderate hepatic impairment monitor ALT, AST, and bilirubin prior to the start of treatment, every week for the first month, every two weeks for the following two months of treatment and monthly thereafter. If elevations in ALT and/or AST greater than 5X upper limit of normal (ULN) or total bilirubin greater than 3X ULN occur in patients with baseline moderate hepatic impairment, discontinue abiraterone acetate tablets and do not re-treat patients with abiraterone acetate tablets [see Use in Specific Populations (8.6)and Clinical Pharmacology (12.3)].

Do not use abiraterone acetate tablets in patients with baseline severe hepatic impairment (Child-Pugh Class C).

Hepatotoxicity

For patients who develop hepatotoxicity during treatment with abiraterone acetate tablets (ALT and/or AST greater than 5X ULN or total bilirubin greater than 3X ULN), interrupt treatment with abiraterone acetate tablets [see Warnings and Precautions (5.3)]. Treatment may be restarted at a reduced dose of 750 mg once daily following return of liver function tests to the patient’s baseline or to AST and ALT less than or equal to 2.5X ULN and total bilirubin less than or equal to 1.5X ULN. For patients who resume treatment, monitor serum transaminases and bilirubin at a minimum of every two weeks for three months and monthly thereafter.

If hepatotoxicity recurs at the dose of 750 mg once daily, re-treatment may be restarted at a reduced dose of 500 mg once daily following return of liver function tests to the patient’s baseline or to AST and ALT less than or equal to 2.5X ULN and total bilirubin less than or equal to 1.5X ULN.

If hepatotoxicity recurs at the reduced dose of 500 mg once daily, discontinue treatment with abiraterone acetate tablets. Permanently discontinue abiraterone acetate tablets for patients who develop a concurrent elevation of ALT greater than 3 x ULN and total bilirubin greater than 2 x ULN in the absence of biliary obstruction or other causes responsible for the concurrent elevation [see Warnings and Precautions (5.3)].

2.5 Dose Modification Guidelines for Strong CYP3A4 Inducers

Avoid concomitant strong CYP3A4 inducers (e.g., phenytoin, carbamazepine, rifampin, rifabutin, rifapentine, phenobarbital) during abiraterone acetate tablets treatment.

If a strong CYP3A4 inducer must be co-administered, increase the abiraterone acetate tablets dosing frequency to twice a day only during the co-administration period (e.g., from 1,000 mg once daily to 1,000 mg twice a day). Reduce the dose back to the previous dose and frequency, if the concomitant strong CYP3A4 inducer is discontinued [see Drug Interactions (7.1)and Clinical Pharmacology (12.3)].

3 DOSAGE FORMS AND STRENGTHS

Abiraterone acetate tablets, USP 250 mg are white to off-white, oval-shaped, uncoated tablets debossed with “AN65” on one side and plain on the other side.

4 CONTRAINDICATIONS

Pregnancy

Abiraterone acetate can cause fetal harm and potential loss of pregnancy [see Use in Specific Populations (8.1)].

5 WARNINGS AND PRECAUTIONS

5.1 Hypertension, Hypokalemia and Fluid Retention Due to Mineralocorticoid Excess

Abiraterone acetate may cause hypertension, hypokalemia, and fluid retention as a consequence of increased mineralocorticoid levels resulting from CYP17 inhibition [see Clinical Pharmacology (12.1)]. Monitor patients for hypertension, hypokalemia, and fluid retention at least once a month. Control hypertension and correct hypokalemia before and during treatment with abiraterone acetate.

In the combined data from 4 placebo-controlled trials using prednisone 5 mg twice daily in combination with 1,000 mg abiraterone acetate daily, grades 3 to 4 hypokalemia were detected in 4% of patients on the abiraterone acetate arm and 2% of patients on the placebo arm. Grades 3 to 4 hypertension were observed in 2% of patients each arm and grades 3 to 4 fluid retention in 1% of patients each arm.

Closely monitor patients whose underlying medical conditions might be compromised by increases in blood pressure, hypokalemia or fluid retention, such as those with heart failure, recent myocardial infarction, cardiovascular disease, or ventricular arrhythmia. The safety of abiraterone acetate in patients with left ventricular ejection fraction <50% or New York Heart Association (NYHA) Class III or IV heart failure (in COU-AA-301) or NYHA Class II to IV heart failure (in COU-AA-302) has not been established because these patients were excluded from these randomized clinical trials [see Clinical Studies (14)].

5.2 Adrenocortical Insufficiency

Adrenal insufficiency occurred in 0.3% of 2,230 patients taking abiraterone acetate and in 0.1% of 1,763 patients taking placebo in the combined data of randomized, placebo-controlled clinical studies. Adrenocortical insufficiency was reported in patients receiving abiraterone acetate in combination with prednisone, following interruption of daily steroids and/or with concurrent infection or stress.

Monitor patients for symptoms and signs of adrenocortical insufficiency, particularly if patients are withdrawn from prednisone, have prednisone dose reductions, or experience unusual stress.

Symptoms and signs of adrenocortical insufficiency may be masked by adverse reactions associated with mineralocorticoid excess seen in patients treated with abiraterone acetate. If clinically indicated, perform appropriate tests to confirm the diagnosis of adrenocortical insufficiency. Increased dosage of corticosteroids may be indicated before, during and after stressful situations [see Warnings and Precautions (5.1)].

5.3 Hepatotoxicity

In postmarketing experience, there have been abiraterone acetate-associated severe hepatic toxicity, including fulminant hepatitis, acute liver failure and deaths [see Adverse Reactions (6.2)].

In the combined data of randomized clinical trials, grade 3 to 4 ALT or AST increases (at least 5X ULN) were reported in 6% of 2,230 patients who received abiraterone acetate, typically during the first 3 months after starting treatment. Patients whose baseline ALT or AST were elevated were more likely to experience liver test elevation than those beginning with normal values. Treatment discontinuation due to ALT and AST increases or abnormal hepatic function occurred in 1.1% of 2,230 patients taking abiraterone acetate. In these clinical trials, no deaths clearly related to abiraterone acetate were reported due to hepatotoxicity events.

Measure serum transaminases (ALT and AST) and bilirubin levels prior to starting treatment with abiraterone acetate, every two weeks for the first three months of treatment and monthly thereafter. In patients with baseline moderate hepatic impairment receiving a reduced abiraterone acetate dose of 250 mg, measure ALT, AST, and bilirubin prior to the start of treatment, every week for the first month, every two weeks for the following two months of treatment and monthly thereafter. Promptly measure serum total bilirubin, AST, and ALT if clinical symptoms or signs suggestive of hepatotoxicity develop. Elevations of AST, ALT, or bilirubin from the patient’s baseline should prompt more frequent monitoring. If at any time AST or ALT rise above five times the ULN, or the bilirubin rises above three times the ULN, interrupt abiraterone acetate treatment and closely monitor liver function.

Re-treatment with abiraterone acetate at a reduced dose level may take place only after return of liver function tests to the patient’s baseline or to AST and ALT less than or equal to 2.5X ULN and total bilirubin less than or equal to 1.5X ULN [see Dosage and Administration (2.4)].

Permanently discontinue abiraterone acetate for patients who develop a concurrent elevation of ALT greater than 3 x ULN and total bilirubin greater than 2 x ULN in the absence of biliary obstruction or other causes responsible for the concurrent elevation [see Dosage and Administration (2.4)].

The safety of abiraterone acetate re-treatment of patients who develop AST or ALT greater than or equal to 20X ULN and/or bilirubin greater than or equal to 10X ULN is unknown.

6 ADVERSE REACTIONS

The following are discussed in more detail in other sections of the labeling:

- Hypertension, Hypokalemia, and Fluid Retention due to Mineralocorticoid Excess [see Warnings and Precautions (5.1)].
- Adrenocortical Insufficiency [see Warnings and Precautions (5.2)].
- Hepatotoxicity [see Warnings and Precautions (5.3)].

6.1 Clinical Trial Experience

Because clinical trials are conducted under widely varying conditions, adverse reaction rates observed in the clinical trials of a drug cannot be directly compared to rates in the clinical trials of another drug and may not reflect the rates observed in clinical practice.

Two randomized placebo-controlled, multicenter clinical trials (COU-AA-301 and COU-AA-302) enrolled patients who had metastatic CRPC in which abiraterone acetate was administered orally at a dose of 1,000 mg daily in combination with prednisone 5 mg twice daily in the active treatment arms. Placebo plus prednisone 5 mg twice daily was given to patients on the control arm. Another randomized placebo-controlled, multicenter clinical trial enrolled patients who had another indication in which abiraterone acetate was administered in combination with prednisone. Placebos were administered to patients in the control arm. Additionally, two other randomized, placebo-controlled trials were conducted in patients with metastatic CRPC. The safety data pooled from 2,230 patients in randomized controlled trials constitute the basis for the data presented in the Warnings and Precautions, Grade 1 to 4 adverse reactions, and Grade 1 to 4 laboratory abnormalities. In all trials, a gonadotropin-releasing hormone (GnRH) analog or prior orchiectomy was required in both arms.

In the pooled data, median treatment duration was 11 months (0.1, 43) for abiraterone acetate-treated patients and 7.2 months (0.1, 43) for placebo-treated patients. The most common adverse reactions (≥10%) that occurred more commonly (>2%) in the abiraterone acetate arm were fatigue, arthralgia, hypertension, nausea, edema, hypokalemia, hot flush, diarrhea, vomiting, upper respiratory infection, cough, and headache. The most common laboratory abnormalities (>20%) that occurred more commonly (≥2%) in the abiraterone acetate arm were anemia, elevated alkaline phosphatase, hypertriglyceridemia, lymphopenia, hypercholesterolemia, hyperglycemia, and hypokalemia. Grades 3 to 4 adverse events were reported for 53% of patients in the abiraterone acetate arm and 46% of patients in the placebo arm. Treatment discontinuation was reported in 14% of patients in the abiraterone acetate arm and 13% of patients in the placebo arm. The common adverse events (≥1%) resulting in discontinuation of abiraterone acetate and prednisone were hepatotoxicity and cardiac disorders.

Deaths associated with treatment-emergent adverse events were reported for 7.5% of patients in the abiraterone acetate arm and 6.6% of patients in the placebo arm. Of the patients in the abiraterone acetate arm, the most common cause of death was disease progression (3.3%). Other reported causes of death in ≥5 patients included pneumonia, cardio-respiratory arrest, death (no additional information), and general physical health deterioration.

COU-AA-301: Metastatic CRPC Following Chemotherapy

COU-AA-301 enrolled 1195 patients with metastatic CRPC who had received prior docetaxel chemotherapy. Patients were not eligible if AST and/or ALT ≥2.5X ULN in the absence of liver metastases. Patients with liver metastases were excluded if AST and/or ALT >5X ULN.

Table 1 shows adverse reactions on the abiraterone acetate arm in COU-AA-301 that occurred with a ≥2% absolute increase in frequency compared to placebo or were events of special interest. The median duration of treatment with abiraterone acetate with prednisone was 8 months.

Table 1: Adverse Reactions due to abiraterone acetate in COU-AA-301
 | Abiraterone Acetate with Prednisone (N=791) |  | Placebo with Prednisone (N=394)
System/Organ Class | All Grades^1 | Grade 3 to 4 | All Grades | Grade 3 to 4
Adverse reaction | % | % | % | %
Musculoskeletal and connective tissue disorders
Joint swelling/discomfort^2 | 30 | 4.2 | 23 | 4.1
Muscle discomfort^3 | 26 | 3.0 | 23 | 2.3
General disorders
Edema^4 | 27 | 1.9 | 18 | 0.8
Vascular disorders
Hot flush | 19 | 0.3 | 17 | 0.3
Hypertension | 8.5 | 1.3 | 6.9 | 0.3
Gastrointestinal disorders
Diarrhea | 18 | 0.6 | 14 | 1.3
Dyspepsia | 6.1 | 0 | 3.3 | 0
Infections and infestations
Urinary tract infection | 12 | 2.1 | 7.1 | 0.5
Upper respiratory tract infection | 5.4 | 0 | 2.5 | 0
Respiratory, thoracic and mediastinal disorders
Cough | 11 | 0 | 7.6 | 0
Renal and urinary disorders
Urinary frequency | 7.2 | 0.3 | 5.1 | 0.3
Nocturia | 6.2 | 0 | 4.1 | 0
Injury, poisoning and procedural complications
Fractures^5 | 5.9 | 1.4 | 2.3 | 0
Cardiac disorders
Arrhythmia^6 | 7.2 | 1.1 | 4.6 | 1.0
Chest pain or chest discomfort^7 | 3.8 | 0.5 | 2.8 | 0
Cardiac failure^8 | 2.3 | 1.9 | 1.0 | 0.3
^1 Adverse events graded according to CTCAE version 3.0.
^2 Includes terms Arthritis, Arthralgia, Joint swelling, and Joint stiffness.
^3 Includes terms Muscle spasms, Musculoskeletal pain, Myalgia, Musculoskeletal discomfort, and Musculoskeletal stiffness.
^4 Includes terms Edema, Edema peripheral, Pitting edema, and Generalized edema.
^5 Includes all fractures with the exception of pathological fracture.
^6 Includes terms Arrhythmia, Tachycardia, Atrial fibrillation, Supraventricular tachycardia, Atrial tachycardia, Ventricular tachycardia, Atrial flutter, Bradycardia, Atrioventricular block complete, Conduction disorder, and Bradyarrhythmia.
^7 Includes terms Angina pectoris, Chest pain, and Angina unstable. Myocardial infarction or ischemia occurred more commonly in the placebo arm than in the abiraterone acetate arm (1.3% vs. 1.1% respectively).
^8 Includes terms Cardiac failure, Cardiac failure congestive, Left ventricular dysfunction, Cardiogenic shock, Cardiomegaly, Cardiomyopathy, and Ejection fraction decreased.

Table 2 shows laboratory abnormalities of interest from COU-AA-301.

Table 2: Laboratory Abnormalities of Interest in COU-AA-301
 | Abiraterone Acetate with Prednisone (N=791) |  | Placebo with Prednisone (N=394)
Laboratory Abnormality | All Grades (%) | Grade 3 to 4 (%) | All Grades (%) | Grade 3 to 4 (%)
Hypertriglyceridemia | 63 | 0.4 | 53 | 0
High AST | 31 | 2.1 | 36 | 1.5
Hypokalemia | 28 | 5.3 | 20 | 1.0
Hypophosphatemia | 24 | 7.2 | 16 | 5.8
High ALT | 11 | 1.4 | 10 | 0.8
High Total Bilirubin | 6.6 | 0.1 | 4.6 | 0

COU-AA-302: Metastatic CRPC Prior to Chemotherapy

COU-AA-302 enrolled 1088 patients with metastatic CRPC who had not received prior cytotoxic chemotherapy. Patients were ineligible if AST and/or ALT ≥2.5X ULN and patients were excluded if they had liver metastases.

Table 3 shows adverse reactions on the abiraterone acetate arm in COU-AA-302 that occurred in ≥5% of patients with a ≥2% absolute increase in frequency compared to placebo. The median duration of treatment with abiraterone acetate with prednisone was 13.8 months.

Table 3: Adverse Reactions in ≥5% of Patients on the Abiraterone Acetate Arm in COU-AA-302
 | Abiraterone Acetate with Prednisone (N=542) |  | Placebo with Prednisone (N=540)
System/Organ Class | All Grades^1 | Grade 3 to 4 | All Grades | Grade 3 to 4
Adverse reaction | % | % | % | %
General disorders
Fatigue | 39 | 2.2 | 34 | 1.7
Edema^2 | 25 | 0.4 | 21 | 1.1
Pyrexia | 8.7 | 0.6 | 5.9 | 0.2
Musculoskeletal and connective tissue disorders
Joint swelling/discomfort^3 | 30 | 2.0 | 25 | 2.0
Groin pain | 6.6 | 0.4 | 4.1 | 0.7
Gastrointestinal disorders
Constipation | 23 | 0.4 | 19 | 0.6
Diarrhea | 22 | 0.9 | 18 | 0.9
Dyspepsia | 11 | 0.0 | 5.0 | 0.2
Vascular disorders
Hot flush | 22 | 0.2 | 18 | 0.0
Hypertension | 22 | 3.9 | 13 | 3.0
Respiratory, thoracic and mediastinal disorders
Cough | 17 | 0.0 | 14 | 0.2
Dyspnea | 12 | 2.4 | 9.6 | 0.9
Psychiatric disorders
Insomnia | 14 | 0.2 | 11 | 0.0
Injury, poisoning and procedural complications
Contusion | 13 | 0.0 | 9.1 | 0.0
Falls | 5.9 | 0.0 | 3.3 | 0.0
Infections and infestations
Upper respiratory tract infection | 13 | 0.0 | 8.0 | 0.0
Nasopharyngitis | 11 | 0.0 | 8.1 | 0.0
Renal and urinary disorders
Hematuria | 10 | 1.3 | 5.6 | 0.6
Skin and subcutaneous tissue disorders
Rash | 8.1 | 0.0 | 3.7 | 0.0
^1 Adverse events graded according to CTCAE version 3.0.
^2 Includes terms Edema peripheral, Pitting edema, and Generalized edema.
^3 Includes terms Arthritis, Arthralgia, Joint swelling, and Joint stiffness.

Table 4 shows laboratory abnormalities that occurred in greater than 15% of patients, and more frequently (>5%) in the abiraterone acetate arm compared to placebo in COU-AA-302.

Table 4: Laboratory Abnormalities in >15% of Patients in the Abiraterone Acetate Arm of COU-AA-302
 | Abiraterone Acetate with Prednisone (N=542) |  | Placebo with Prednisone (N=540)
Laboratory Abnormality | Grade 1 to 4 | Grade 3 to 4 | Grade 1 to 4 | Grade 3 to 4
Laboratory Abnormality | % | % | % | %
Hematology
Lymphopenia | 38 | 8.7 | 32 | 7.4
Chemistry
Hyperglycemia^1 | 57 | 6.5 | 51 | 5.2
High ALT | 42 | 6.1 | 29 | 0.7
High AST | 37 | 3.1 | 29 | 1.1
Hypernatremia | 33 | 0.4 | 25 | 0.2
Hypokalemia | 17 | 2.8 | 10 | 1.7
^1 Based on non-fasting blood draws

Cardiovascular Adverse Reactions

In the combined data of randomized, placebo-controlled clinical studies, cardiac failure occurred more commonly in patients on the abiraterone acetate arm compared to patients on the placebo arm (2.6% versus 0.9%). Grade 3 to 4 cardiac failure occurred in 1.3% of patients taking abiraterone acetate and led to 5 treatment discontinuations and 4 deaths. Grade 3 to 4 cardiac failure occurred in 0.2% of patients taking placebo. There were no treatment discontinuations and two deaths due to cardiac failure in the placebo group.

In the same combined data, the majority of arrhythmias were grade 1 or 2. There was one death associated with arrhythmia and three patients with sudden death in the abiraterone acetate arms and five deaths in the placebo arms. There were 7 (0.3%) deaths due to cardiorespiratory arrest in the abiraterone acetate arms and 2 (0.1%) deaths in the placebo arms. Myocardial ischemia or myocardial infarction led to death in 3 patients in the placebo arms and 3 deaths in the abiraterone acetate arms.

6.2 Postmarketing Experience

The following additional adverse reactions have been identified during post approval use of abiraterone acetate with prednisone. Because these reactions are reported voluntarily from a population of uncertain size, it is not always possible to reliably estimate their frequency or establish a causal relationship to drug exposure.

Respiratory, Thoracic and Mediastinal Disorders: non-infectious pneumonitis.

Musculoskeletal and Connective Tissue Disorders: myopathy, including rhabdomyolysis.

Hepatobiliary Disorders: fulminant hepatitis, including acute hepatic failure and death.

To report SUSPECTED ADVERSE REACTIONS contact AvKARE, Inc. at 1-855-361-3993; email
drugsafety@avkare.com; or FDA at 1-800-FDA-1088 or www.fda.gov/medwatch.

7 DRUG INTERACTIONS

7.1 Drugs that Inhibit or Induce CYP3A4 Enzymes

Based on in vitro data, abiraterone acetate is a substrate of CYP3A4.

In a dedicated drug interaction trial, co-administration of rifampin, a strong CYP3A4 inducer, decreased exposure of abiraterone by 55%. Avoid concomitant strong CYP3A4 inducers during abiraterone acetate treatment. If a strong CYP3A4 inducer must be co-administered, increase the abiraterone acetate dosing frequency [see Dosage and Administration (2.5)and Clinical Pharmacology (12.3)].

In a dedicated drug interaction trial, co-administration of ketoconazole, a strong inhibitor of CYP3A4, had no clinically meaningful effect on the pharmacokinetics of abiraterone [see Clinical Pharmacology (12.3)].

7.2 Effects of Abiraterone on Drug Metabolizing Enzymes

Abiraterone acetate is an inhibitor of the hepatic drug-metabolizing enzymes CYP2D6 and CYP2C8. In a CYP2D6 drug-drug interaction trial, the Cmax and AUC of dextromethorphan (CYP2D6 substrate) were increased 2.8- and 2.9-fold, respectively, when dextromethorphan was given with abiraterone acetate 1,000 mg daily and prednisone 5 mg twice daily. Avoid co-administration of abiraterone acetate with substrates of CYP2D6 with a narrow therapeutic index (e.g., thioridazine). If alternative treatments cannot be used, consider a dose reduction of the concomitant CYP2D6 substrate drug [see Clinical Pharmacology (12.3)].

In a CYP2C8 drug-drug interaction trial in healthy subjects, the AUC of pioglitazone (CYP2C8 substrate) was increased by 46% when pioglitazone was given together with a single dose of 1,000 mg abiraterone acetate. Therefore, patients should be monitored closely for signs of toxicity related to a CYP2C8 substrate with a narrow therapeutic index if used concomitantly with abiraterone acetate [see Clinical Pharmacology (12.3)].

8 USE IN SPECIFIC POPULATIONS

8.1 Pregnancy

Risk Summary

Based on findings from animal studies and the mechanism of action, abiraterone acetate is contraindicated for use in pregnant women because the drug can cause fetal harm and potential loss of pregnancy. Abiraterone acetate is not indicated for use in females.

There are no human data on the use of abiraterone acetate in pregnant women. In animal reproduction studies, oral administration of abiraterone acetate to pregnant rats during organogenesis caused adverse developmental effects at maternal exposures approximately ≥ 0.03 times the human exposure (AUC) at the recommended dose (see Data).

Data

Animal Data

In an embryo-fetal developmental toxicity study in rats, abiraterone acetate caused developmental toxicity when administered at oral doses of 10, 30 or 100 mg/kg/day throughout the period of organogenesis (gestational days 6 to 17). Findings included embryo-fetal lethality (increased post implantation loss and resorptions and decreased number of live fetuses), fetal developmental delay (skeletal effects) and urogenital effects (bilateral ureter dilation) at doses ≥10 mg/kg/day, decreased fetal ano-genital distance at ≥30 mg/kg/day, and decreased fetal body weight at 100 mg/kg/day. Doses ≥10 mg/kg/day caused maternal toxicity. The doses tested in rats resulted in systemic exposures (AUC) approximately 0.03, 0.1 and 0.3 times, respectively, the AUC in patients.

8.2 Lactation

Risk Summary

Abiraterone acetate is not indicated for use in women. There is no information available on the presence of abiraterone acetate in human milk, or on the effects on the breastfed child or milk production.

8.3 Females and Males of Reproductive Potential

Contraception

Males

Based on findings in animal reproduction studies and its mechanism of action, advise males with female partners of reproductive potential to use effective contraception during treatment and for 3 weeks after the final dose of abiraterone acetate [see Use in Specific Populations (8.1)].

Infertility

Based on animal studies, abiraterone acetate may impair reproductive function and fertility in males of reproductive potential [see Nonclinical Toxicology (13.1)].

8.4 Pediatric Use

Safety and effectiveness of abiraterone acetate in pediatric patients have not been established.

8.5 Geriatric Use

Of the total number of patients receiving abiraterone acetate in randomized clinical trials, 70% of patients were 65 years and over and 27% were 75 years and over. No overall differences in safety or effectiveness were observed between these elderly patients and younger patients. Other reported clinical experience has not identified differences in responses between the elderly and younger patients, but greater sensitivity of some older individuals cannot be ruled out.

8.6 Patients with Hepatic Impairment

The pharmacokinetics of abiraterone were examined in subjects with baseline mild (N=8) or moderate (N=8) hepatic impairment (Child-Pugh Class A and B, respectively) and in 8 healthy control subjects with normal hepatic function. The systemic exposure (AUC) of abiraterone after a single oral 1,000 mg dose of abiraterone acetate increased by approximately 1.1-fold and 3.6-fold in subjects with mild and moderate baseline hepatic impairment, respectively compared to subjects with normal hepatic function.

In another trial, the pharmacokinetics of abiraterone were examined in subjects with baseline severe (N=8) hepatic impairment (Child-Pugh Class C) and in 8 healthy control subjects with normal hepatic function. The systemic exposure (AUC) of abiraterone increased by approximately 7-fold and the fraction of free drug increased 2-fold in subjects with severe baseline hepatic impairment compared to subjects with normal hepatic function.

No dosage adjustment is necessary for patients with baseline mild hepatic impairment. In patients with baseline moderate hepatic impairment (Child-Pugh Class B), reduce the recommended dose of abiraterone acetate to 250 mg once daily. Do not use abiraterone acetate in patients with baseline severe hepatic impairment (Child-Pugh Class C). If elevations in ALT or AST >5X ULN or total bilirubin >3X ULN occur in patients with baseline moderate hepatic impairment, discontinue abiraterone acetate treatment [see Dosage and Administration (2.4)and Clinical Pharmacology (12.3)].

For patients who develop hepatotoxicity during treatment, interruption of treatment and dosage adjustment may be required [see Dosage and Administration (2.4), Warnings and Precautions (5.3), and Clinical Pharmacology (12.3)].

8.7 Patients with Renal Impairment

No dosage adjustment is necessary for patients with renal impairment [see Clinical Pharmacology (12.3)].

10 OVERDOSAGE

Human experience of overdose with abiraterone acetate is limited.

There is no specific antidote. In the event of an overdose, stop abiraterone acetate, undertake general supportive measures, including monitoring for arrhythmias and cardiac failure and assess liver function.

11 DESCRIPTION

Abiraterone acetate USP, the active ingredient of abiraterone acetate tablets, USP is the acetyl ester of abiraterone. Abiraterone is an inhibitor of CYP17 (17α-hydroxylase/C17,20-lyase). Each abiraterone acetate tablet, USP contains 250 mg of abiraterone acetate, USP. Abiraterone acetate, USP is designated chemically as (3β)-17-(3-pyridinyl) androsta-5,16-dien-3-yl acetate and its structure is:

Abiraterone acetate, USP is a white to off-white, non-hygroscopic, crystalline powder. Its molecular formula is C26H33NO2 and it has a molecular weight of 391.55. Abiraterone acetate, USP is a lipophilic compound with an octanol-water partition coefficient of 5.12 (Log P) and is practically insoluble in water. The pKa of the aromatic nitrogen is 5.19.

Inactive ingredients in the tablets are colloidal silicon dioxide, croscarmellose sodium, lactose monohydrate, magnesium stearate, microcrystalline cellulose, povidone, and sodium lauryl sulfate.

USP dissolution test pending.

12 CLINICAL PHARMACOLOGY

12.1 Mechanism of Action

Abiraterone acetate is converted in vivo to abiraterone, an androgen biosynthesis inhibitor, that inhibits 17 α-hydroxylase/C17,20-lyase (CYP17). This enzyme is expressed in testicular, adrenal, and prostatic tumor tissues and is required for androgen biosynthesis.

CYP17 catalyzes two sequential reactions: 1) the conversion of pregnenolone and progesterone to their 17α-hydroxy derivatives by 17α-hydroxylase activity and 2) the subsequent formation of dehydroepiandrosterone (DHEA) and androstenedione, respectively, by C17, 20 lyase activity. DHEA and androstenedione are androgens and are precursors of testosterone. Inhibition of CYP17 by abiraterone can also result in increased mineralocorticoid production by the adrenals [see Warnings and Precautions (5.1)].

Androgen sensitive prostatic carcinoma responds to treatment that decreases androgen levels. Androgen deprivation therapies, such as treatment with GnRH agonists or orchiectomy, decrease androgen production in the testes but do not affect androgen production by the adrenals or in the tumor.

Abiraterone acetate decreased serum testosterone and other androgens in patients in the placebo-controlled clinical trial. It is not necessary to monitor the effect of abiraterone acetate on serum testosterone levels.

Changes in serum prostate specific antigen (PSA) levels may be observed but have not been shown to correlate with clinical benefit in individual patients.

12.3 Pharmacokinetics

Following administration of abiraterone acetate, the pharmacokinetics of abiraterone and abiraterone acetate have been studied in healthy subjects and in patients with metastatic CRPC. In vivo, abiraterone acetate is converted to abiraterone. In clinical studies, abiraterone acetate plasma concentrations were below detectable levels (<0.2 ng/mL) in >99% of the analyzed samples.

Absorption

Following oral administration of abiraterone acetate to patients with metastatic CRPC, the median time to reach maximum plasma abiraterone concentrations is 2 hours. Abiraterone accumulation is observed at steady-state, with a 2-fold higher exposure (steady-state AUC) compared to a single 1,000 mg dose of abiraterone acetate.

At the dose of 1,000 mg daily in patients with metastatic CRPC, steady-state values (mean ± SD) of Cmax were 226 ± 178 ng/mL and of AUC were 993 ± 639 ng.hr/mL. No major deviation from dose proportionality was observed in the dose range of 250 mg to 1,000 mg. However, the exposure was not significantly increased when the dose was doubled from 1,000 to 2,000 mg (8% increase in the mean AUC).

Systemic exposure of abiraterone is increased when abiraterone acetate is administered with food. In healthy subjects abiraterone Cmax and AUC0-∞ were approximately 7- and 5-fold higher, respectively, when a single dose of abiraterone acetate was administered with a low-fat meal (7% fat, 300 calories) and approximately 17- and 10-fold higher, respectively, when a single dose of abiraterone acetate was administered with a high-fat (57% fat, 825 calories) meal compared to overnight fasting. Abiraterone AUC0-∞ was approximately 7-fold or 1.6-fold higher, respectively, when a single dose of abiraterone acetate was administered 2 hours after or 1 hour before a medium fat meal (25% fat, 491 calories) compared to overnight fasting.

Systemic exposures of abiraterone in patients with metastatic CRPC, after repeated dosing of abiraterone acetate were similar when abiraterone acetate was taken with low-fat meals for 7 days and increased approximately 2-fold when taken with high-fat meals for 7 days compared to when taken at least 2 hours after a meal and at least 1 hour before a meal for 7 days.

Given the normal variation in the content and composition of meals, taking abiraterone acetate with meals has the potential to result in increased and highly variable exposures. Therefore, abiraterone acetate must be taken on an empty stomach, either one hour before or two hours after a meal. The tablets should be swallowed whole with water [see Dosage and Administration (2.3)].

Distribution and Protein Binding

Abiraterone is highly bound (>99%) to the human plasma proteins, albumin and alpha-1 acid glycoprotein. The apparent steady-state volume of distribution (mean ± SD) is 19,669 ± 13,358 L. In vitro studies show that at clinically relevant concentrations, abiraterone acetate and abiraterone are not substrates of P-glycoprotein (P-gp) and that abiraterone acetate is an inhibitor of P-gp.

Metabolism

Following oral administration of^14C-abiraterone acetate as capsules, abiraterone acetate is hydrolyzed to abiraterone (active metabolite). The conversion is likely through esterase activity (the esterases have not been identified) and is not CYP mediated. The two main circulating metabolites of abiraterone in human plasma are abiraterone sulphate (inactive) and N-oxide abiraterone sulphate (inactive), which account for about 43% of exposure each. CYP3A4 and SULT2A1 are the enzymes involved in the formation of N-oxide abiraterone sulphate and SULT2A1 is involved in the formation of abiraterone sulphate.

Excretion

In patients with metastatic CRPC, the mean terminal half-life of abiraterone in plasma (mean ± SD) is 12 ± 5 hours. Following oral administration of^14C-abiraterone acetate, approximately 88% of the radioactive dose is recovered in feces and approximately 5% in urine. The major compounds present in feces are unchanged abiraterone acetate and abiraterone (approximately 55% and 22% of the administered dose, respectively).

Patients with Hepatic Impairment

The pharmacokinetics of abiraterone was examined in subjects with baseline mild (N=8) or moderate (N=8) hepatic impairment (Child-Pugh Class A and B, respectively) and in 8 healthy control subjects with normal hepatic function. Systemic exposure to abiraterone after a single oral 1,000 mg dose given under fasting conditions increased approximately 1.1-fold and 3.6-fold in subjects with mild and moderate baseline hepatic impairment, respectively. The mean half-life of abiraterone is prolonged to approximately 18 hours in subjects with mild hepatic impairment and to approximately 19 hours in subjects with moderate hepatic impairment.

In another trial, the pharmacokinetics of abiraterone were examined in subjects with baseline severe (N=8) hepatic impairment (Child-Pugh Class C) and in 8 healthy control subjects with normal hepatic function. The systemic exposure (AUC) of abiraterone increased by approximately 7-fold in subjects with severe baseline hepatic impairment compared to subjects with normal hepatic function. In addition, the mean protein binding was found to be lower in the severe hepatic impairment group compared to the normal hepatic function group, which resulted in a two-fold increase in the fraction of free drug in patients with severe hepatic impairment [see Dosage and Administration (2.4)and Use in Specific Populations (8.6)].

Patients with Renal Impairment

The pharmacokinetics of abiraterone were examined in patients with end-stage renal disease (ESRD) on a stable hemodialysis schedule (N=8) and in matched control subjects with normal renal function (N=8). In the ESRD cohort of the trial, a single 1,000 mg abiraterone acetate dose was given under fasting conditions 1 hour after dialysis, and samples for pharmacokinetic analysis were collected up to 96 hours post dose. Systemic exposure to abiraterone after a single oral 1,000 mg dose did not increase in subjects with end-stage renal disease on dialysis, compared to subjects with normal renal function [see Use in Specific Populations (8.7)].

Drug Interactions

In vitro studies with human hepatic microsomes showed that abiraterone has the potential to inhibit CYP1A2, CYP2D6, CYP2C8 and to a lesser extent CYP2C9, CYP2C19 and CYP3A4/5.

In an in vivo drug-drug interaction trial, the Cmax and AUC of dextromethorphan (CYP2D6 substrate) were increased 2.8- and 2.9-fold, respectively when dextromethorphan 30 mg was given with abiraterone acetate 1,000 mg daily (plus prednisone 5 mg twice daily). The AUC for dextrorphan, the active metabolite of dextromethorphan, increased approximately 1.3 fold [see Drug Interactions (7.2)].

In a clinical study to determine the effects of abiraterone acetate 1,000 mg daily (plus prednisone 5 mg twice daily) on a single 100 mg dose of the CYP1A2 substrate theophylline, no increase in systemic exposure of theophylline was observed.

Abiraterone is a substrate of CYP3A4, in vitro. In a clinical pharmacokinetic interaction study of healthy subjects pretreated with a strong CYP3A4 inducer (rifampin, 600 mg daily for 6 days) followed by a single dose of abiraterone acetate 1,000 mg, the mean plasma AUC∞ of abiraterone was decreased by 55% [see Drug Interactions (7.1)].

In a separate clinical pharmacokinetic interaction study of healthy subjects, co-administration of ketoconazole, a strong inhibitor of CYP3A4, had no clinically meaningful effect on the pharmacokinetics of abiraterone [see Drug Interactions (7.1)].

In a CYP2C8 drug-drug interaction trial in healthy subjects, the AUC of pioglitazone was increased by 46% when pioglitazone was given together with a single dose of 1,000 mg abiraterone acetate [see Drug Interactions (7.2)].

In vitro, abiraterone and its major metabolites were shown to inhibit the hepatic uptake transporter OATP1B1. There are no clinical data available to confirm transporter based interaction.

12.6 QT Prolongation

In a multi-center, open-label, single-arm trial, 33 patients with metastatic CRPC received abiraterone acetate orally at a dose of 1,000 mg once daily at least 1 hour before or 2 hours after a meal in combination with prednisone 5 mg orally twice daily. Assessments up to Cycle 2 Day 2 showed no large changes in the QTc interval (i.e., >20 ms) from baseline. However, small increases in the QTc interval (i.e., <10 ms) due to abiraterone acetate cannot be excluded due to study design limitations.

13 NONCLINICAL TOXICOLOGY

13.1 Carcinogenesis, Mutagenesis, and Impairment of Fertility

A two-year carcinogenicity study was conducted in rats at oral abiraterone acetate doses of 5, 15, and 50 mg/kg/day for males and 15, 50, and 150 mg/kg/day for females. Abiraterone acetate increased the combined incidence of interstitial cell adenomas and carcinomas in the testes at all dose levels tested. This finding is considered to be related to the pharmacological activity of abiraterone. Rats are regarded as more sensitive than humans to developing interstitial cell tumors in the testes. Abiraterone acetate was not carcinogenic in female rats at exposure levels up to 0.8 times the human clinical exposure based on AUC. Abiraterone acetate was not carcinogenic in a 6-month study in the transgenic (Tg.rasH2) mouse.

Abiraterone acetate and abiraterone was not mutagenic in an in vitro microbial mutagenesis (Ames) assay or clastogenic in an in vitro cytogenetic assay using primary human lymphocytes or an in vivo rat micronucleus assay.

In repeat-dose toxicity studies in male rats (13- and 26-weeks) and monkeys (39-weeks), atrophy, aspermia/hypospermia, and hyperplasia in the reproductive system were observed at ≥50 mg/kg/day in rats and ≥250 mg/kg/day in monkeys and were consistent with the antiandrogenic pharmacological activity of abiraterone. These effects were observed in rats at systemic exposures similar to humans and in monkeys at exposures approximately 0.6 times the AUC in humans.

In a fertility study in male rats, reduced organ weights of the reproductive system, sperm counts, sperm motility, altered sperm morphology and decreased fertility were observed in animals dosed for 4 weeks at ≥30 mg/kg/day orally. Mating of untreated females with males that received 30 mg/kg/day oral abiraterone acetate resulted in a reduced number of corpora lutea, implantations and live embryos and an increased incidence of pre-implantation loss. Effects on male rats were reversible after 16 weeks from the last abiraterone acetate administration.

In a fertility study in female rats, animals dosed orally for 2 weeks until day 7 of pregnancy at ≥30 mg/kg/day had an increased incidence of irregular or extended estrous cycles and pre-implantation loss (300 mg/kg/day). There were no differences in mating, fertility, and litter parameters in female rats that received abiraterone acetate. Effects on female rats were reversible after 4 weeks from the last abiraterone acetate administration.

The dose of 30 mg/kg/day in rats is approximately 0.3 times the recommended dose of 1,000 mg/day based on body surface area.

In 13- and 26-week studies in rats and 13- and 39-week studies in monkeys, a reduction in circulating testosterone levels occurred with abiraterone acetate at approximately one half the human clinical exposure based on AUC. As a result, decreases in organ weights and toxicities were observed in the male and female reproductive system, adrenal glands, liver, pituitary (rats only), and male mammary glands. The changes in the reproductive organs are consistent with the antiandrogenic pharmacological activity of abiraterone acetate.

13.2 Animal Toxicology and/or Pharmacology

A dose-dependent increase in cataracts was observed in rats after daily oral abiraterone acetate administration for 26 weeks starting at ≥50 mg/kg/day (similar to the human clinical exposure based on AUC). In a 39-week monkey study with daily oral abiraterone acetate administration, no cataracts were observed at higher doses (2 times greater than the clinical exposure based on AUC).

17 PATIENT COUNSELING INFORMATION

Advise the patient to read the FDA-approved patient labeling (Patient Information)

Hypertension, Hypokalemia, and Fluid Retention

- Inform patients that abiraterone acetate is associated with hypertension, hypokalemia, and peripheral edema. Advise patients to report symptoms of hypertension, hypokalemia, or edema to their healthcare provider [see Warnings and Precautions (5.1)].
  Adrenocortical Insufficiency
- Inform patients that abiraterone acetate with prednisone is associated with adrenal insufficiency. Advise patients to report symptoms of adrenocortical insufficiency to their healthcare provider [see Warnings and Precautions (5.2)].
  Hepatotoxicity
- Inform patients that abiraterone acetate is associated with severe hepatotoxicity. Inform patients that their liver function will be monitored using blood tests. Advise patients to immediately report symptoms of hepatotoxicity to their healthcare provider [see Warnings and Precautions (5.3)].
  Dosing and Administration
- Inform patients that abiraterone acetate is taken once daily with prednisone (twice daily according to their healthcare provider’s instructions) and to not interrupt or stop either of these medications without consulting their healthcare provider.
- Inform patients receiving GnRH therapy that they need to maintain this treatment during the course of treatment with abiraterone acetate.
- Instruct patients to take abiraterone acetate on an empty stomach, either one hour before or two hours after a meal. Abiraterone acetate taken with food causes increased exposure and may result in adverse reactions. Instruct patients to swallow tablets whole with water and not to crush or chew the tablets [see Dosage and Administration (2.3)].
- Inform patients that if they miss a dose of abiraterone acetate or prednisone, they should take their normal dose the following day. If more than one daily dose is skipped, inform patients to contact their healthcare provider [see Dosage and Administration (2.3)].

Fetal Toxicity

- Inform patients that abiraterone acetate may harm a developing fetus. Advise males with female partners of reproductive potential to use effective contraception during treatment and for 3 weeks after the final dose of abiraterone acetate [see Use in Specific Populations (8.1)].
- Women who are pregnant or women who may be pregnant should not handle abiraterone acetate 250 mg tablets or other abiraterone acetate tablets if broken, crushed, or damaged without protection, e.g., gloves [see Use in Specific Populations (8.1)and How Supplied/Storage and Handling (16)].

Infertility

- Advise male patients that abiraterone acetate may impair fertility [see Use in Specific Populations (8.3)].

Manufactured for:
AvKARE
Pulaski, TN 38478
Mfg. Rev. 10-2018-01
AV 12/18 (P)

14 CLINICAL STUDIES

The efficacy and safety of abiraterone acetate with prednisone was established in three randomized placebo-controlled international clinical studies. All patients in these studies received a GnRH analog or had prior bilateral orchiectomy. Patients with prior ketoconazole treatment for prostate cancer and a history of adrenal gland or pituitary disorders were excluded from these trials. Concurrent use of spironolactone was not allowed during the study period.

COU-AA-301 (NCT00638690): Patients with metastatic CRPC who had received prior docetaxel chemotherapy

A total of 1195 patients were randomized 2:1 to receive either abiraterone acetate orally at a dose of 1,000 mg once daily in combination with prednisone 5 mg orally twice daily (N=797) or placebo once daily plus prednisone 5 mg orally twice daily (N=398). Patients randomized to either arm were to continue treatment until disease progression (defined as a 25% increase in PSA over the patient’s baseline/nadir together with protocol-defined radiographic progression and symptomatic or clinical progression), initiation of new treatment, unacceptable toxicity or withdrawal.

The following patient demographics and baseline disease characteristics were balanced between the treatment arms. The median age was 69 years (range 39 to 95) and the racial distribution was 93% Caucasian, 3.6% Black, 1.7% Asian, and 1.6% Other. Eighty-nine percent of patients enrolled had an ECOG performance status score of 0 to 1 and 45% had a Brief Pain Inventory-Short Form score of ≥4 (patient’s reported worst pain over the previous 24 hours). Ninety percent of patients had metastases in bone and 30% had visceral involvement. Seventy percent of patients had radiographic evidence of disease progression and 30% had PSA-only progression. Seventy percent of patients had previously received one cytotoxic chemotherapy regimen and 30% received two regimens.

The protocol pre-specified interim analysis was conducted after 552 deaths and showed a statistically significant improvement in overall survival (OS) in patients treated with abiraterone acetate with prednisone compared to patients in the placebo with prednisone arm (Table 9 and Figure 1). An updated survival analysis was conducted when 775 deaths (97% of the planned number of deaths for final analysis) were observed. Results from this analysis were consistent with those from the interim analysis (Table 7).

Table 7: Overall Survival of Patients Treated with Either Abiraterone Acetate or Placebo in Combination with Prednisone in COU-AA-301 (Intent-to-Treat Analysis)
 | Abiraterone Acetate with Prednisone (N=797) | Placebo with Prednisone (N=398)
Primary Survival Analysis
Deaths (%) | 333 (42%) | 219 (55%)
Median survival (months) | 14.8 (14.1, 15.4) | 10.9 (10.2, 12.0)
(95% CI)
p-value^1 | <0.0001
Hazard ratio (95% CI)^2 | 0.646 (0.543, 0.768)
Updated Survival Analysis
Deaths (%) | 501 (63%) | 274 (69%)
Median survival (months) | 15.8 (14.8, 17.0) | 11.2 (10.4, 13.1)
(95% CI)
Hazard ratio (95% CI)^2 | 0.740 (0.638, 0.859)
^1 p-value is derived from a log-rank test stratified by ECOG performance status score (0 to 1 vs. 2), pain score (absent vs. present), number of prior chemotherapy regimens (1 vs. 2), and type of disease progression (PSA only vs. radiographic).
^2 Hazard Ratio is derived from a stratified proportional hazards model. Hazard ratio <1 favors abiraterone acetate with prednisone.

Figure 1: Kaplan-Meier Overall Survival Curves in COU-AA-301 (Intent-to-Treat Analysis)

COU-AA-302 (NCT00887198): Patients with metastatic CRPC who had not received prior cytotoxic chemotherapy

In COU-AA-302, 1,088 patients were randomized 1:1 to receive either abiraterone acetate orally at a dose of 1,000 mg once daily (N=546) or Placebo orally once daily (N=542). Both arms were given concomitant prednisone 5 mg twice daily. Patients continued treatment until radiographic or clinical (cytotoxic chemotherapy, radiation or surgical treatment for cancer, pain requiring chronic opioids, or ECOG performance status decline to 3 or more) disease progression, unacceptable toxicity or withdrawal. Patients with moderate or severe pain, opiate use for cancer pain, or visceral organ metastases were excluded.

Patient demographics were balanced between the treatment arms. The median age was 70 years. The racial distribution of patients treated with abiraterone acetate was 95% Caucasian, 2.8% Black, 0.7% Asian and 1.1% Other. The ECOG performance status was 0 for 76% of patients, and 1 for 24% of patients. Co-primary efficacy endpoints were overall survival and radiographic progression-free survival (rPFS). Baseline pain assessment was 0 to 1 (asymptomatic) in 66% of patients and 2 to 3 (mildly symptomatic) in 26% of patients as defined by the Brief Pain Inventory-Short Form (worst pain over the last 24 hours).

Radiographic progression-free survival was assessed with the use of sequential imaging studies and was defined by bone scan identification of 2 or more new bone lesions with confirmation (Prostate Cancer Working Group 2 criteria) and/or modified Response Evaluation Criteria In Solid Tumors (RECIST) criteria for progression of soft tissue lesions. Analysis of rPFS utilized centrally-reviewed radiographic assessment of progression.

The planned final analysis for OS, conducted after 741 deaths (median follow up of 49 months) demonstrated a statistically significant OS improvement in patients treated with abiraterone acetate with prednisone compared to those treated with placebo with prednisone (Table 8 and Figure 2). Sixty-five percent of patients on the abiraterone acetate arm and 78% of patients on the placebo arm used subsequent therapies that may prolong OS in metastatic CRPC. Abiraterone acetate was used as a subsequent therapy in 13% of patients on the abiraterone acetate arm and 44% of patients on the placebo arm.

Table 8: Overall Survival of Patients Treated with Either Abiraterone Acetate or Placebo in Combination with Prednisone in COU-AA-302 (Intent-to-Treat Analysis)
Overall Survival | Abiraterone Acetate with Prednisone (N=546) | Placebo with Prednisone (N=542)
Deaths | 354 (65%) | 387 (71%)
Median survival (months) (95% CI) | 34.7 (32.7, 36.8) | 30.3 (28.7, 33.3)
p-value^1 | 0.0033
Hazard ratio^2 (95% CI) | 0.81 (0.70, 0.93)
^1 p-value is derived from a log-rank test stratified by ECOG performance status score (0 vs. 1).
^2 Hazard Ratio is derived from a stratified proportional hazards model. Hazard ratio <1 favors abiraterone acetate with prednisone.

Figure 2: Kaplan Meier Overall Survival Curves in COU-AA-302

At the pre-specified rPFS analysis, 150 (28%) patients treated with abiraterone acetate with prednisone and 251 (46%) patients treated with placebo with prednisone had radiographic progression. A significant difference in rPFS between treatment groups was observed (Table 9 and Figure 3).

Table 9: Radiographic Progression-free Survival of Patients Treated with Either Abiraterone Acetate or Placebo in Combination with Prednisone in COU-AA-302 (Intent-to-Treat Analysis)
Radiographic Progression-free Survival | Abiraterone Acetate with Prednisone (N=546) | Placebo with Prednisone (N=542)
Progression or death | 150 (28%) | 251 (46%)
Median rPFS (months) (95% CI) | NR (11.66, NR) | 8.28 (8.12, 8.54)
p-value^1 | <0.0001
Hazard ratio^2 (95% CI) | 0.425 (0.347, 0.522)
NR=Not reached.
^1 p-value is derived from a log-rank test stratified by ECOG performance status score (0 vs. 1).
^2 Hazard Ratio is derived from a stratified proportional hazards model. Hazard ratio <1 favors abiraterone acetate with prednisone.

Figure 3: Kaplan Meier Curves of Radiographic Progression-free Survival in COU-AA-302 (Intent-to-Treat Analysis)

The primary efficacy analyses are supported by the following prospectively defined endpoints. The median time to initiation of cytotoxic chemotherapy was 25.2 months for patients in the abiraterone acetate arm and 16.8 months for patients in the placebo arm (HR=0.580; 95% CI: [0.487, 0.691], p < 0.0001).

The median time to opiate use for prostate cancer pain was not reached for patients receiving abiraterone acetate and was 23.7 months for patients receiving placebo (HR=0.686; 95% CI: [0.566, 0.833], p=0.0001). The time to opiate use result was supported by a delay in patient reported pain progression favoring the abiraterone acetate arm.

16 HOW SUPPLIED/STORAGE AND HANDLING

Abiraterone acetate tablets are available in the strengths and packages listed below:

Abiraterone acetate tablets, USP, 250 mg, are available as white to off-white, oval-shaped, uncoated tablets and debossed with “AN65” on one side and plain on the other side. They are supplied as follows:

Bottles of 120: NDC 42291-024-12

Storage and Handling

Store at 20° to 25°C (68° to 77°F); excursions permitted between 15° to 30°C (59° to 86°F) [see USP Controlled Room Temperature].

Keep out of reach of children.

Based on its mechanism of action, abiraterone acetate tablets may harm a developing fetus. Women who are pregnant or women who may be pregnant should not handle abiraterone acetate tablets or other abiraterone acetate tablets if broken, crushed, or damaged without protection, e.g., gloves [see Use in Specific Populations (8.1)] .

PATIENT INFORMATION

Abiraterone Acetate (aʺ bir aʹ ter one asʹ e tate) Tablets, USP

Read this Patient Information that comes with abiraterone acetate tablets before you start taking it and each time you get a refill. There may be new information. This information does not take the place of talking with your healthcare provider about your medical condition or your treatment.

What are abiraterone acetate tablets?

Abiraterone acetate tablets are a prescription medicine that is used along with prednisone. Abiraterone acetate tablets are used to treat men with prostate cancer that has spread to other parts of the body.

Abiraterone acetate tablets are not for use in women.

It is not known if abiraterone acetate tablets are safe or effective in children.

Who should not take abiraterone acetate tablets?

Abiraterone acetate tablets are not for use in women.

Do not take abiraterone acetate tablets if you are pregnant or may become pregnant. Abiraterone acetate tablets may harm your unborn baby. Women who are pregnant or who may become pregnant should not touch abiraterone acetate tablets or other abiraterone acetate tablets if broken, crushed, or damaged without protection, such as gloves.

What should I tell my healthcare provider before taking abiraterone acetate tablets?

Before you take abiraterone acetate tablets, tell your healthcare provider if you:

- have heart problems
- have liver problems
- have a history of adrenal problems
- have a history of pituitary problems
- have any other medical conditions
- plan to become pregnant. See “Who should not take abiraterone acetate tablets?”
- are breastfeeding or plan to breastfeed. It is not known if abiraterone acetate passes into your breast milk. You and your healthcare provider should decide if you will take abiraterone acetate tablets or breastfeed. You should not do both. See “Who should not take abiraterone acetate tablets?”

Tell your healthcare provider about all the medicines you take, including prescription and over-the-counter medicines, vitamins, and herbal supplements. Abiraterone acetate tablets can interact with many other medicines.

You should not start or stop any medicine before you talk with the healthcare provider that prescribed abiraterone acetate tablets.

Know the medicines you take. Keep a list of them with you to show to your healthcare provider and pharmacist when you get a new medicine.

How should I take abiraterone acetate tablets?

- Take abiraterone acetate tablets and prednisone exactly as your healthcare provider tells you.
- Take your prescribed dose of abiraterone acetate tablets 1 time a day.
- Your healthcare provider may change your dose if needed.
- Do not stop taking your prescribed dose of abiraterone acetate tablets or prednisone without talking with your healthcare provider first.
- Take abiraterone acetate tablets on an empty stomach, either one hour before or two hours after a meal. Do not take abiraterone acetate tablets with food. Taking abiraterone acetate tablets with food may cause more of the medicine to be absorbed by the body than is needed and this may cause side effects.
- Swallow abiraterone acetate tablets whole. Do not crush or chew tablets.
- Take abiraterone acetate tablets with water.
- Men who are sexually active with a pregnant woman must use a condom during and for 3 weeks after treatment with abiraterone acetate tablets. If their female partner may become pregnant, a condom and another form of birth control must be used during and for 3 weeks after treatment with abiraterone acetate tablets. Talk with your healthcare provider if you have questions about birth control.
- If you miss a dose of abiraterone acetate tablets or prednisone, take your prescribed dose the following day. If you miss more than 1 dose, tell your healthcare provider right away.

- Your healthcare provider will do blood tests to check for side effects.

What are the possible side effects of abiraterone acetate tablets?

Abiraterone acetate tablets may cause serious side effects including:

- High blood pressure (hypertension), low blood potassium levels (hypokalemia) and fluid retention (edema). Tell your healthcare provider if you get any of the following symptoms:
  - dizziness
  - fast heartbeats
  - feel faint or lightheaded
  - headache
  - confusion
  - muscle weakness
  - pain in your legs
  - swelling in your legs or feet
  - Adrenal problems may happen if you stop taking prednisone, get an infection, or are under stress.
  - Liver problems. You may develop changes in liver function blood test. Your healthcare provider will do blood tests to check your liver before treatment with abiraterone acetate tablets and during treatment with abiraterone acetate tablets. Liver failure may occur, which can lead to death. Tell your healthcare provider if you notice any of the following changes:
  - yellowing of the skin or eyes
  - darkening of the urine
  - severe nausea or vomiting
  The most common side effects of abiraterone acetate tablets include:
  - feeling very tired
  - joint pain
  - high blood pressure
  - nausea
  - swelling in your legs or feet
  - low blood potassium levels
  - hot flushes
  - diarrhea
  - vomiting
  - infected nose, sinuses, or throat (cold)
  - cough
  - headache
  - low red blood cells (anemia)
  - high blood cholesterol and triglycerides
  - high blood sugar levels
  - certain other abnormal blood tests
  Tell your healthcare provider if you have any side effect that bothers you or that does not go away.
  These are not all the possible side effects of abiraterone acetate tablets. For more information, ask your healthcare provider or pharmacist.
  Call your doctor for medical advice about side effects. You may report side effects to FDA at 1-800-FDA-1088.

How should I store abiraterone acetate tablets?

- Store abiraterone acetate tablets at room temperature between 68°F to 77°F (20°C to 25°C).

Keep abiraterone acetate tablets and all medicines out of the reach of children.

General information about abiraterone acetate tablets.

Medicines are sometimes prescribed for purposes other than those listed in a Patient Information leaflet.

Do not use abiraterone acetate tablets for a condition for which it was not prescribed. Do not give abiraterone acetate tablets to other people, even if they have the same symptoms that you have. It may harm them.

This leaflet summarizes the most important information about abiraterone acetate tablets. If you would like more information, talk with your healthcare provider. You can ask your healthcare provider or pharmacist for information about abiraterone acetate tablets that is written for health professionals.

For more information, call AvKARE at 1-855-361-3993 or go to www.avkare.com.

What are the ingredients of abiraterone acetate tablets?

Active ingredient: abiraterone acetate, USP

Inactive ingredients: colloidal silicon dioxide, croscarmellose sodium, lactose monohydrate, magnesium stearate, microcrystalline cellulose, povidone, and sodium lauryl sulfate.

Manufactured for:
AvKARE
Pulaski, TN 38478
Mfg. Rev. 10-2018-01
AV 12/18 (P)

This Patient Information has been approved by the U.S. Food and Drug Administration. Rev. 11-2018-01